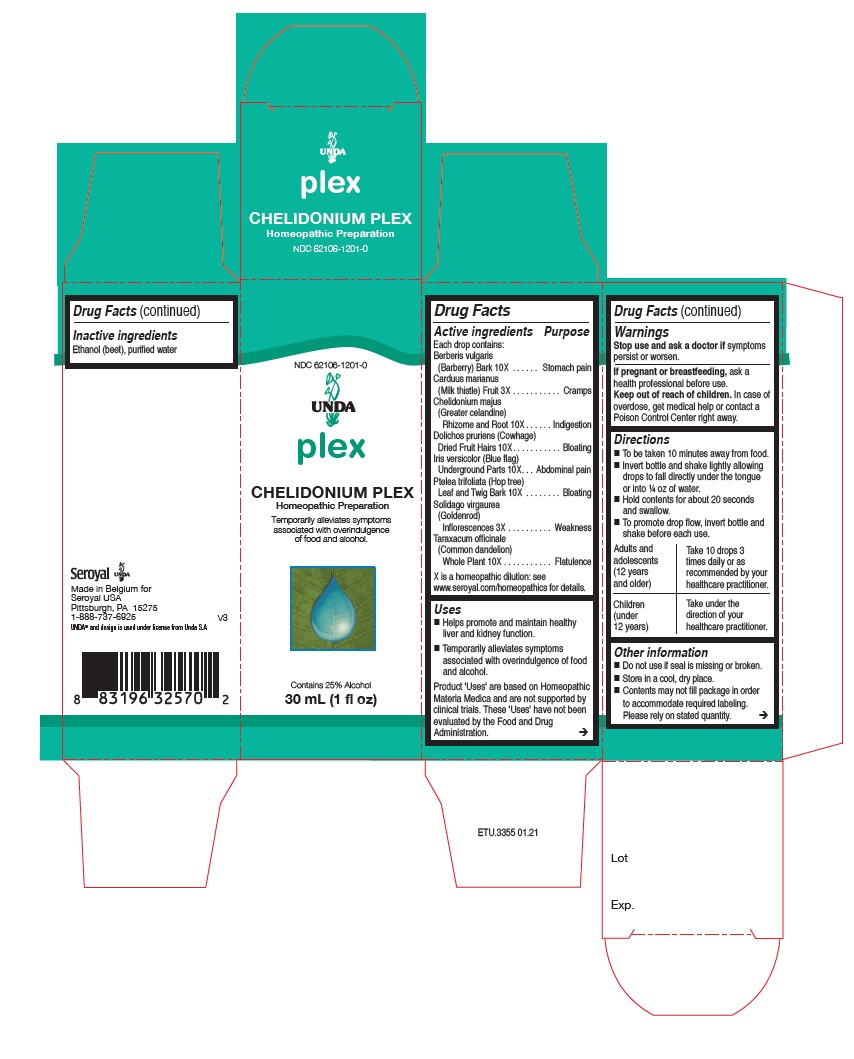 DRUG LABEL: Chelidonium Plex
NDC: 62106-1201 | Form: LIQUID
Manufacturer: Seroyal USA
Category: homeopathic | Type: HUMAN OTC DRUG LABEL
Date: 20210714

ACTIVE INGREDIENTS: PTELEA TRIFOLIATA BARK 10 [hp_X]/30 mL; TARAXACUM OFFICINALE 10 [hp_X]/30 mL; BERBERIS VULGARIS ROOT BARK 10 [hp_X]/30 mL; MUCUNA PRURIENS FRUIT TRICHOME 10 [hp_X]/30 mL; IRIS VERSICOLOR ROOT 10 [hp_X]/30 mL; CHELIDONIUM MAJUS 10 [hp_X]/30 mL; MILK THISTLE 3 [hp_X]/30 mL; SOLIDAGO VIRGAUREA FLOWERING TOP 3 [hp_X]/30 mL
INACTIVE INGREDIENTS: ALCOHOL; WATER

Chelidonium Plex

Active ingredients

Each drop contains:

Berberis vulgaris (Barberry) Bark 10X
Carduus marianus (Milk thistle) Fruit 3X
Chelidonium majus (Greater celandine) Rhizome and Root 10X
Dolichos pruriens (Cowhage) Dried Fruit Hairs 10X
Iris versicolor (Blue flag) Underground Parts 10X
Ptelea trifoliata (Hop tree) Leaf and Twig Bark 10X
Solidago virgaurea (Goldenrod) Inflorescences 3X
Taraxacum officinale (Common dandelion) Whole Plant 10X

Uses
Helps promote and maintain healthy liver and kidney function.
Temporarily alleviates symptoms associated with overindulgence of food and alcohol.

Warnings
Stop use and ask a doctor if symptoms persist or worsen.
If pregnant or breastfeeding, ask a health professional before use.
Keep out of reach of children.

In case of overdose, get medical help or contact a Poison Control Center right away.

PREGNANCY OR BREAST FEEDING

If pregnant or breastfeeding, ask a health professional before use.

Keep out of reach of children.

OVERDOSAGE

In case of overdose, get medical help or contact a Poison Control Center right away.

Inactive ingredients
Ethanol (beet), purified water

Directions:

To be taken ten minutes away from food.

Children: Divided dosage by half and follow adult directions.

Invert bottle and shake lightly allowing for drops to fall directly under the tongue or into 1/4 oz. of water.

Hold contents for about 20 seconds and swallow.

To promote drop flow, invert bottle and shake before each use.

Adults and adolescents (12 years and older)

Take 10 drops three times daily or as recommended by your healthcare practitioner.

Children (under 12 years)

Take under the direction of your healthcare practitioner.

Uses
Helps promote and maintain healthy liver and kidney function.
Temporarily alleviates symptoms associated with overindulgence of food and alcohol.

Directions

To be taken ten minutes away from food.

Invert bottle and shake lightly allowing for drops to fall directly under the tongue or into 1/4 oz. of water.

Hold contents for about 20 seconds and swallow.

To promote drop flow, invert bottle and shake before each use.

Adults and adolescents (12 years and older)

Take 10 drops three times daily or as recommended by your healthcare practitioner.

Children (under 12 years)

Take under the direction of your healthcare practitioner.

Other information
Do not use if seal is missing or broken.
Store in a cool, dry place.

Contents may not fill package in order to accommodate required labeling. Please rely on stated quantity.

PACKAGE LABEL

NDC 62106-1201-0

UNDA

plex

CHELIDONIUM PLEX

Homeopathic Preparation

Temporarily alleviates symptoms
associated with overindulgence
of food and alcohol.

Contains 25% Alcohol
1 fl oz (30 mL)